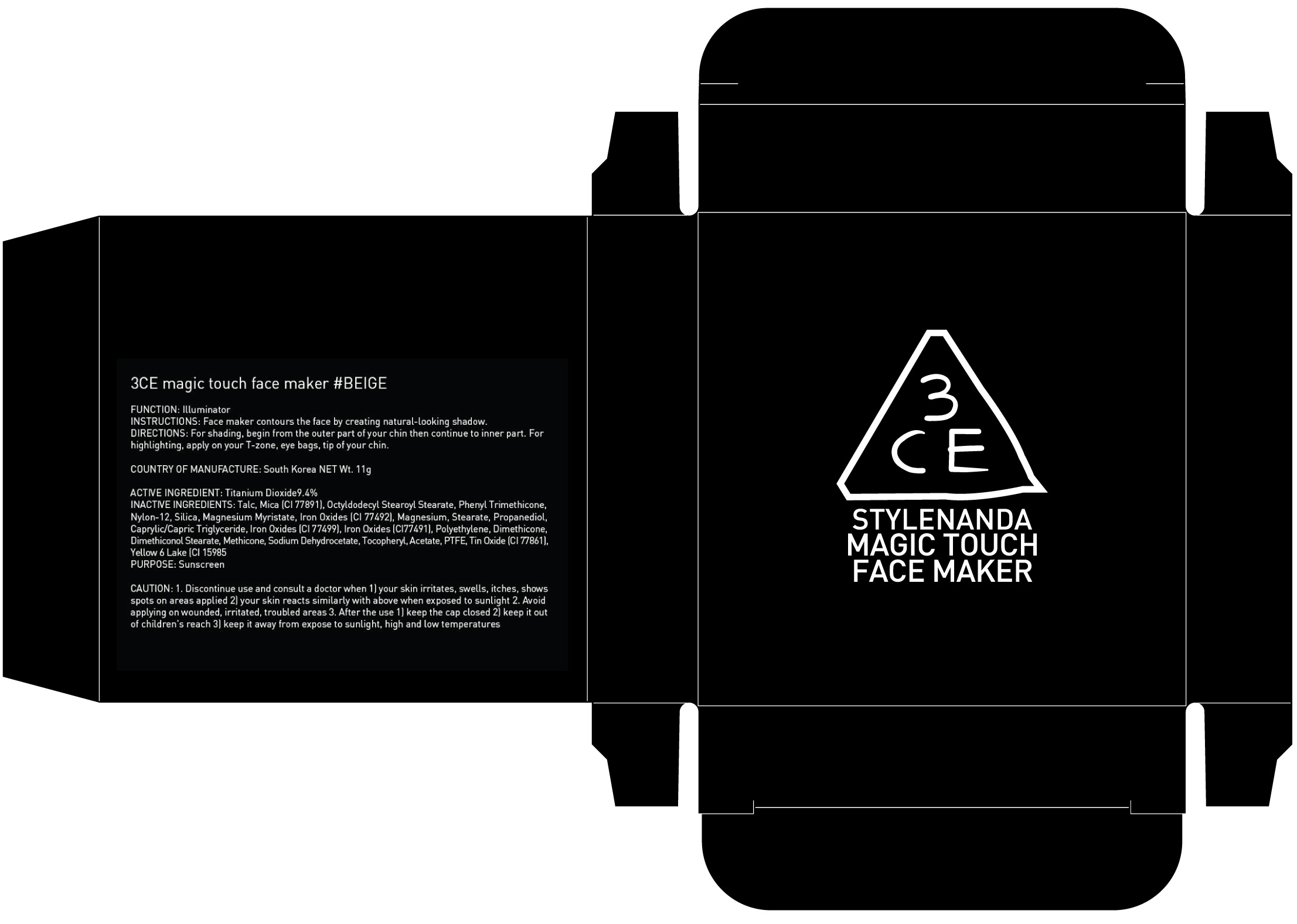 DRUG LABEL: 3CE MAGIC TOUCH FACE MAKER BEIGE
NDC: 60764-016 | Form: POWDER
Manufacturer: Nanda Co., Ltd
Category: otc | Type: HUMAN OTC DRUG LABEL
Date: 20160921

ACTIVE INGREDIENTS: Titanium Dioxide 1.03 g/11 g
INACTIVE INGREDIENTS: Talc; Mica

ACTIVE INGREDIENT

Active Ingredient: Titanium Dioxide 9.4%

INACTIVE INGREDIENT

Inactive Ingredients:

A) Talc, Mica (CI 77019), OctyldodecylStearoyl Stearate, Phenyl Trimethicone, Nylon-12, Silica, Magnesium Myristate, Magnesium Stearate, Caprylic/Capric Triglyceride, Dimethiconol Stearate, Methylparaben, Dimethicone, Methicone, Tin Oxide (CI 77861), Tocopheryl Acetate, Yellow 5 Lake (CI 19140), Propylparaben, Red 30 (CI 73360), Iron Oxides (CI 77499)

B) Talc, Mica (CI 77019), Nylon-12, OctyldodecylStearoyl Stearate, Phenyl Trimethicone, Titanium Dioxide (CI 77891), Silica, Magnesium Myristate, Iron Oxides (CI 77492), Iron Oxides (CI 77499), Iron Oxides (CI 77491), Caprylic/Capric Triglyceride, Magnesium Stearate, Dimethicone, Dimethiconol Stearate, Methicone, Methylparaben, Tocopheryl Acetate, Propylparaben

PURPOSE

Purpose: Sunscreen

CAUTION

CAUTION: 1. Discontinue use and consult a doctor when - your skin irritates, swells, itches, shows spots on areas applied - your skin reacts similarly with above when exposed to sunlight 2. Avoid applying on wounded, irritated, troubled areas 3. After the use - keep the cap closed - keep it out of children's reach - keep it away from expose to sunlight, high and low temperatures

DESCRIPTION

INSTRUCTIONS: Face maker contours the face by creating natural-looking shadow.

Directions: For shading, begin from the outer part of your chin then continue to inner part. For highlighting, apply on your T-zone, eye bags, tip of your chin.